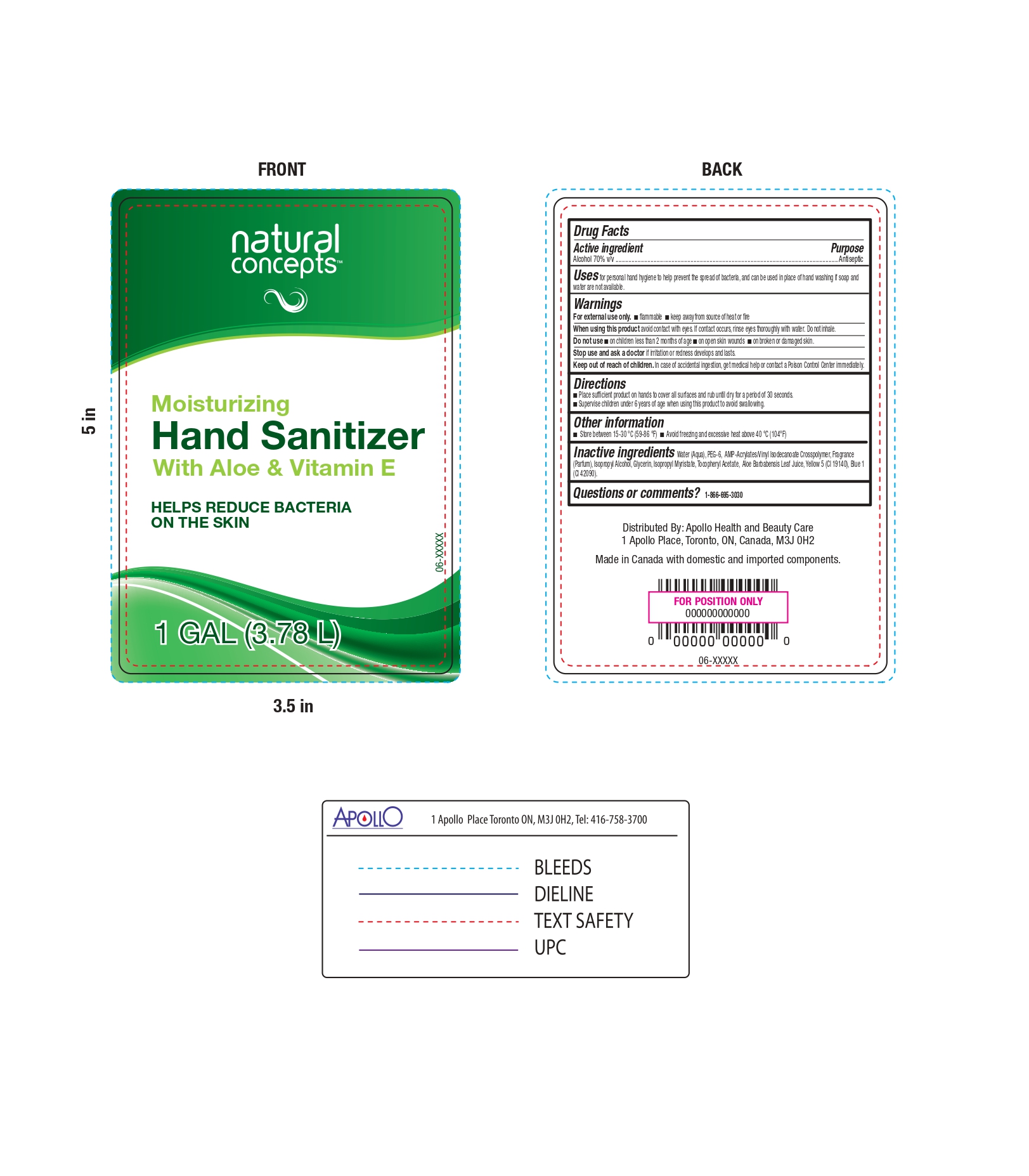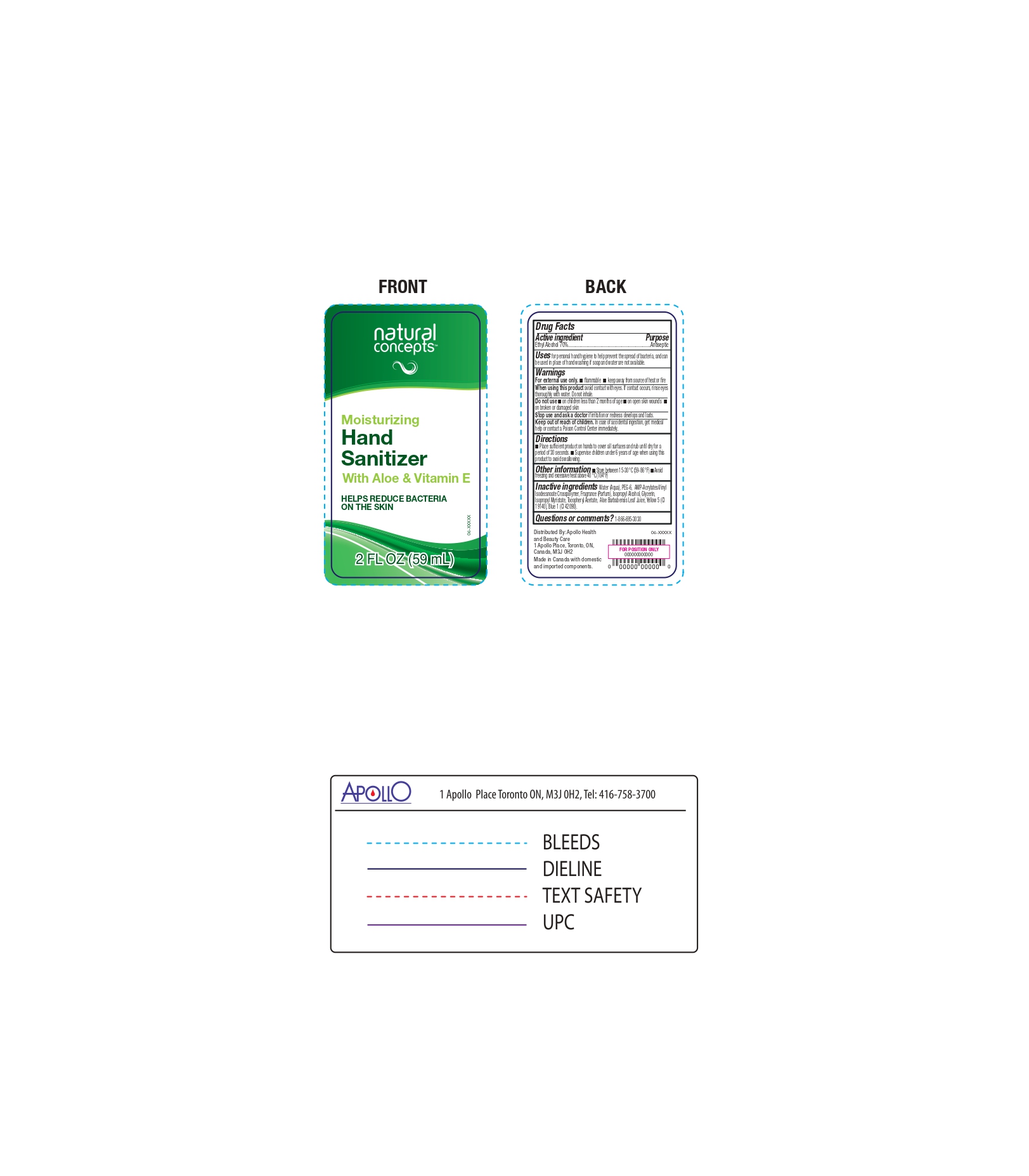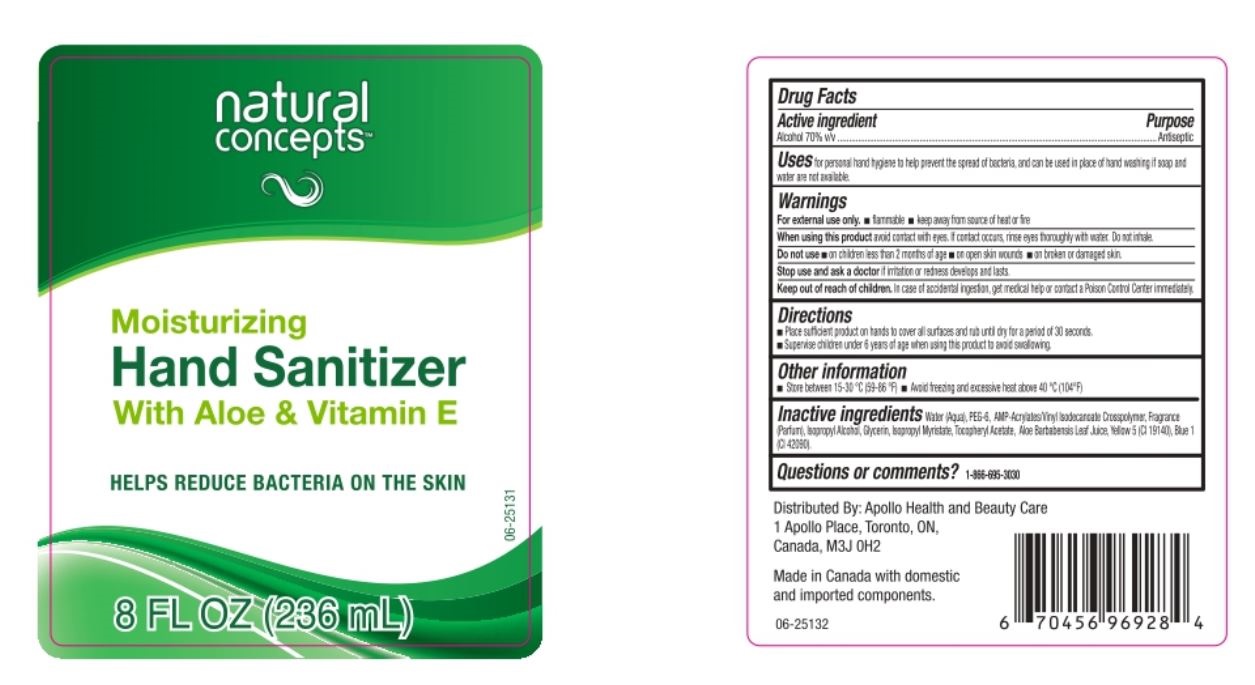 DRUG LABEL: Hand Sanitizer
NDC: 63148-632 | Form: GEL
Manufacturer: Apollo Health and Beauty Care
Category: otc | Type: HUMAN OTC DRUG LABEL
Date: 20250104

ACTIVE INGREDIENTS: ALCOHOL 70 mL/100 mL
INACTIVE INGREDIENTS: ISOPROPYL ALCOHOL; FRAGRANCE CLEAN ORC0600327; ISOPROPYL MYRISTATE; ACRYLATES/VINYL ISODECANOATE CROSSPOLYMER (10000 MPA.S NEUTRALIZED AT 0.5%); ALOE VERA LEAF; .ALPHA.-TOCOPHEROL ACETATE; POLYETHYLENE GLYCOL 300; BASIC BLUE 1; BASIC YELLOW 5; GLYCERIN; WATER

NDC- 63148-632, Natural Concepts Hand Sanitizer

Active Ingredient(s)

Alcohol 70% v/v.

Purpose

Antiseptic

Uses

For personal hand hygiene to help prevent the spread of bacteria, and can be used in place of hand washing if soap and water are not available.

Warnings

- For external use only.
- Flammable.
- Keep away from source of heat or fire.

When using this Product

Avoid contact with eyes. If contact occurs, rinse eyes thoroughly with water. Do not inhale.

Do not use

- on children less than 2 months of age.
- on open skin wounds.
- on broken or dsamaged skin.

Stop use and ask a doctor

If irritation or redness develops and lasts.

Keep out of reach of children

In case of accidental ingestion, get medical help or contact a Poison Control Center immediately.

Directions

- Place sufficient product on hands to cover all surfaces and rub until dry for a period of 30 seconds.
- Supervise children under 6 years of age when using this product to avoid swallowing.

Other information

- Store between 15-30°C (59-86°F)
- Avoid freezing and excessive heat above 40°C (104°F)

Inactive ingredients

Water (Aqua), PEG-6, AMP-Acrylates/Vinyl Isodecanoate Crosspolymer, Fragrance (Parfum), Isopropyl Alcohol, Glycerin, Isopropyl Myristate, Tocopheryl Acetate, Aloe Barbadensis Leaf Juice, Yellow 5 (Cl 19140), Blue 1 (Cl 42090)

Questions or comments?

1-866-695-3030